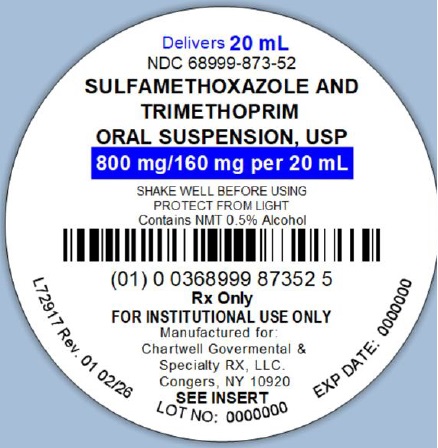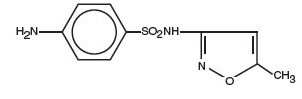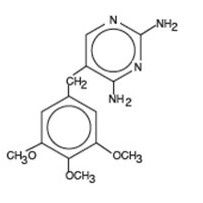 DRUG LABEL: Sulfamethoxazole and Trimethoprim
NDC: 68999-873 | Form: SUSPENSION
Manufacturer: Chartwell Governmental & Specialty RX, LLC.
Category: prescription | Type: HUMAN PRESCRIPTION DRUG LABEL
Date: 20260224

ACTIVE INGREDIENTS: SULFAMETHOXAZOLE 800 mg/20 mL; TRIMETHOPRIM 160 mg/20 mL
INACTIVE INGREDIENTS: ALCOHOL; METHYLPARABEN; SODIUM BENZOATE; ANHYDROUS CITRIC ACID; FD&C RED NO. 40; FD&C YELLOW NO. 6; GLYCERIN; MICROCRYSTALLINE CELLULOSE; POLYSORBATE 80; WATER; SACCHARIN SODIUM; CARBOXYMETHYLCELLULOSE SODIUM, UNSPECIFIED; TRISODIUM CITRATE DIHYDRATE; SORBITOL SOLUTION

Sulfamethoxazole and Trimethoprim Oral Suspension
Rx Only

To reduce the development of drug-resistant bacteria and maintain the effectiveness of sulfamethoxazole and trimethoprim oral suspension and other antibacterial drugs, sulfamethoxazole and trimethoprim oral suspension should be used only to treat or prevent infections that are proven or strongly suspected to be caused by bacteria.

DESCRIPTION

Sulfamethoxazole and Trimethoprim Oral Suspension, USP is a synthetic antibacterial combination product with each teaspoonful (5 mL) containing 200 mg sulfamethoxazole and 40 mg trimethoprim.

Sulfamethoxazole is N^1-(5-methyl-3-isoxazolyl) sulfanilamide; the molecular formula is C10H11N3O3S. It is an almost white, odorless, tasteless compound with a molecular weight of 253.28 and the following structural formula:

Trimethoprim is 2,4-diamino-5-(3,4,5-trimethoxybenzyl) pyrimidine; the molecular formula is C14H18N4O3. It is a white to light yellow, odorless, bitter compound with a molecular weight of 290.3 and the following structural formula:

Each teaspoonful (5 mL) of sulfamethoxazole and trimethoprim oral suspension (cherry flavor) is an opaque pinkish orange suspension with a cherry aroma and contains 40 mg trimethoprim and 200 mg sulfamethoxazole and the inactive ingredients alcohol not more than 0.5%; methylparaben 0.1% and sodium benzoate 0.1% (added as preservatives), artificial wild cherry flavor, citric acid anhydrous, FD&C Red #40, FD&C Yellow #6, glycerin, microcrystalline cellulose, polysorbate 80, purified water, saccharin sodium, sodium carboxymethylcellulose, sodium citrate dihydrate, and sorbitol solution.

CLINICAL PHARMACOLOGY

Sulfamethoxazole and trimethoprim is rapidly absorbed following oral administration. Both sulfamethoxazole and trimethoprim exist in the blood as unbound, protein-bound and metabolized forms; sulfamethoxazole also exists as the conjugated form. Sulfamethoxazole is metabolized in humans to at least 5 metabolites: the N4-acetyl-, N4-hydroxy-, 5-methylhydroxy-, N4-acetyl-5-methylhydroxy- sulfamethoxazole metabolites, and an N-glucuronide conjugate. The formation of N4-hydroxy metabolite is mediated via CYP2C9.

Trimethoprim is metabolized in vitro to 11 different metabolites, of which, five are glutathione adducts and six are oxidative metabolites, including the major metabolites, 1- and 3-oxides and the 3- and 4-hydroxy derivatives.

The free forms of sulfamethoxazole and trimethoprim are considered to be the therapeutically active forms.

In vitro studies suggest that trimethoprim is a substrate of P-glycoprotein, OCT1 and OCT2, and that sulfamethoxazole is not a substrate of P-glycoprotein.

Approximately 70% of sulfamethoxazole and 44% of trimethoprim are bound to plasma proteins. The presence of 10 mg percent sulfamethoxazole in plasma decreases the protein binding of trimethoprim by an insignificant degree; trimethoprim does not influence the protein binding of sulfamethoxazole.

Peak blood levels for the individual components occur 1 to 4 hours after oral administration. The mean serum half-lives of sulfamethoxazole and trimethoprim are 10 and 8 to 10 hours, respectively. However, patients with severely impaired renal function exhibit an increase in the half-lives of both components, requiring dosage regimen adjustment (see DOSAGE AND ADMINISTRATION). Detectable amounts of sulfamethoxazole and trimethoprim are present in the blood 24 hours after drug administration. During administration of 800 mg sulfamethoxazole and 160 mg trimethoprim b.i.d., the mean steady-state plasma concentration of trimethoprim was 1.72 mcg/mL. The steady-state mean plasma levels of free and total sulfamethoxazole were 57.4 mcg/mL and 68 mcg/mL, respectively. These steady-state levels were achieved after three days of drug administration.^1 Excretion of sulfamethoxazole and trimethoprim is primarily by the kidneys through both glomerular filtration and tubular secretion. Urine concentrations of both sulfamethoxazole and trimethoprim are considerably higher than are the concentrations in the blood. The average percentage of the dose recovered in urine from 0 to 72 hours after a single oral dose of sulfamethoxazole and trimethoprim is 84.5% for total sulfonamide and 66.8% for free trimethoprim. Thirty percent of the total sulfonamide is excreted as free sulfamethoxazole, with the remaining as N4-acetylated metabolite.^2 When administered together as sulfamethoxazole and trimethoprim, neither sulfamethoxazole nor trimethoprim affects the urinary excretion pattern of the other.

Both sulfamethoxazole and trimethoprim distribute to sputum, vaginal fluid and middle ear fluid; trimethoprim also distributes to bronchial secretion, and both pass the placental barrier and are excreted in human milk.

Pharmacokinetics in Pediatric Patients

A simulation conducted with data from a pharmacokinetic study in 153 infants and children demonstrated that mean steady state AUC and maximum plasma concentration of trimethoprim and sulfamethoxazole would be comparable between pediatric patients 2 months to 18 years receiving 8/40 (trimethoprim/sulfamethoxazole) mg/kg/day divided every 12 hours and adult patients receiving 320/1600 (trimethoprim/sulfamethoxazole) mg/day.

Pharmacokinetics in Geriatric Patients

The pharmacokinetics of sulfamethoxazole 800 mg and trimethoprim 160 mg were studied in 6 geriatric subjects (mean age: 78.6 years) and 6 young healthy subjects (mean age: 29.3 years) using a non-US approved formulation. Pharmacokinetic values for sulfamethoxazole in geriatric subjects were similar to those observed in young adult subjects. The mean renal clearance of trimethoprim was significantly lower in geriatric subjects compared with young adult subjects (19 mL/h/kg vs. 55 mL/h/kg). However, after normalizing by body weight, the apparent total body clearance of trimethoprim was on average 19% lower in geriatric subjects compared with young adult subjects.^3

Microbiology

Mechanism of Action

Sulfamethoxazole inhibits bacterial synthesis of dihydrofolic acid by competing with para-aminobenzoic acid (PABA). Trimethoprim blocks the production of tetrahydrofolic acid from dihydrofolic acid by binding to and reversibly inhibiting the required enzyme, dihydrofolate reductase. Thus, sulfamethoxazole and trimethoprim blocks two consecutive steps in the biosynthesis of nucleic acids and proteins essential to many bacteria.

Resistance

In vitro studies have shown that bacterial resistance develops more slowly with both sulfamethoxazole and trimethoprim in combination than with either sulfamethoxazole or trimethoprim alone.

Antimicrobial Activity

Sulfamethoxazole and trimethoprim has been shown to be active against most isolates of the following microorganisms, both in vitro and in clinical infections as described in the INDICATIONS AND USAGEsection.

Aerobic gram-positive bacteria

Streptococcus pneumoniae

Aerobic gram-negative bacteria

Escherichia coli (including susceptible enterotoxigenic strains implicated in traveler’s diarrhea)

Klebsiella species

Enterobacter species

Haemophilus influenzae

Morganella morganii

Proteus mirabilis

Proteus vulgaris

Shigella flexneri

Shigella sonnei

Other Microorganisms

Pneumocystis jirovecii

Susceptibility Testing

For specific information regarding susceptibility test interpretive criteria and associated test methods and quality control standards recognized by FDA for this drug, please see: https://www.fda.gov/STIC.

INDICATIONS AND USAGE

To reduce the development of drug-resistant bacteria and maintain the effectiveness of sulfamethoxazole and trimethoprim oral suspension and other antibacterial drugs, sulfamethoxazole and trimethoprim oral suspension should be used only to treat or prevent infections that are proven or strongly suspected to be caused by susceptible bacteria. When culture and susceptibility information are available, they should be considered in selecting or modifying antibacterial therapy. In the absence of such data, local epidemiology and susceptibility patterns may contribute to empiric selection of therapy.

Urinary Tract Infections

For the treatment of urinary tract infections due to susceptible strains of the following organisms: Escherichia coli, Klebsiella species, Enterobacter species, Morganella morganii, Proteus mirabilis and Proteus vulgaris. It is recommended that initial episodes of uncomplicated urinary tract infections be treated with a single effective antibacterial agent rather than the combination.

Acute Otitis Media

For the treatment of acute otitis media in pediatric patients due to susceptible strains of Streptococcus pneumoniae or Haemophilus influenzaewhen in the judgment of the physician sulfamethoxazole and trimethoprim offers some advantage over the use of other antimicrobial agents. To date, there are limited data on the safety of repeated use of sulfamethoxazole and trimethoprim in pediatric patients under two years of age. Sulfamethoxazole and trimethoprim is not indicated for prophylactic or prolonged administration in otitis media at any age.

Acute Exacerbations of Chronic Bronchitis in Adults

For the treatment of acute exacerbations of chronic bronchitis due to susceptible strains of Streptococcus pneumoniae or Haemophilus influenzaewhen a physician deems that sulfamethoxazole and trimethoprim could offer some advantage over the use of a single antimicrobial agent.

Shigellosis

For the treatment of enteritis caused by susceptible strains of Shigella flexneri and Shigella sonnei when antibacterial therapy is indicated.

Pneumocystis jirovecii Pneumonia

For the treatment of documented Pneumocystis jirovecii pneumonia and for prophylaxis against P. jirovecii pneumonia in individuals who are immunosuppressed and considered to be at an increased risk of developing P. jirovecii pneumonia.

Traveler’s Diarrhea in Adults

For the treatment of traveler’s diarrhea due to susceptible strains of enterotoxigenic E. coli.

CONTRAINDICATIONS

Sulfamethoxazole and trimethoprim is contraindicated in the following situations:

- known hypersensitivity to trimethoprim or sulfonamides
- history of drug-induced immune thrombocytopenia with use of trimethoprim and/or sulfonamides
- documented megaloblastic anemia due to folate deficiency
- pediatric patients less than 2 months of age
- marked hepatic damage
- severe renal insufficiency when renal function status cannot be monitored
- concomitant administration with dofetilide (see PRECAUTIONS).

WARNINGS

Embryofetal Toxicity

Some epidemiologic studies suggest that exposure to sulfamethoxazole and trimethoprim during pregnancy may be associated with an increased risk of congenital malformations, particularly neural tube defects, cardiovascular malformations, urinary tract defects, oral clefts, and club foot. If sulfamethoxazole and trimethoprim is used during pregnancy, or if the patient becomes pregnant while taking this drug, the patient should be advised of the potential hazards to the fetus (see PRECAUTIONS).

Hypersensitivity and Other Serious or Fatal Reactions

Fatalities and serious adverse reactions including severe cutaneous adverse reactions (SCARs) including Stevens-Johnson syndrome, toxic epidermal necrolysis, drug reaction with eosinophilia and systemic symptoms (DRESS), acute febrile neutrophilic dermatosis (AFND), acute generalized exanthematous pustulosis (AGEP); fulminant hepatic necrosis; agranulocytosis, aplastic anemia and other blood dyscrasias; acute and delayed lung injury; anaphylaxis and circulatory shock have occurred with the administration of sulfamethoxazole and trimethoprim products, including sulfamethoxazole and trimethoprim oral suspension (see ADVERSE REACTIONS).

Hypersensitivity Reactions of the Respiratory Tract

Cough, shortness of breath and pulmonary infiltrates potentially representing hypersensitivity reactions of the respiratory tract have been reported in association with sulfamethoxazole and trimethoprim treatment.

Respiratory Failure

Other severe pulmonary adverse reactions occurring within days to week of sulfamethoxazole and trimethoprim initiation and resulting in prolonged respiratory failure requiring mechanical ventilation or extracorporeal membrane oxygenation (ECMO), lung transplantation or death have also been reported in patients and otherwise healthy individuals treated with sulfamethoxazole and trimethoprim products

Circulatory Shock

Circulatory shock with fever, severe hypotension, and confusion requiring intravenous fluid resuscitation and vasopressors has occurred within minutes to hours of re-challenge with sulfamethoxazole and trimethoprim products, including sulfamethoxazole and trimethoprim, in patients with history of recent (days to weeks) exposure to sulfamethoxazole and trimethoprim.

Management of Hypersensitivity and Other Serious Reactions

Sulfamethoxazole and trimethoprim should be discontinued at the first appearance of skin rash or any sign of a serious adverse reaction. A skin rash may be followed by a more severe reaction, such as Stevens-Johnson syndrome, toxic epidermal necrolysis, DRESS, AFND, AGEP, hepatic necrosis, or serious blood disorders (see PRECAUTIONSand ADVERSE REACTIONS). Clinical signs, such as rash, pharyngitis, fever, arthralgia, cough, chest pain, dyspnea, pallor, purpura or jaundice may be early indications of serious reactions.

Hemophagocytic Lymphohistiocytosis

Cases of hemophagocytic lymphohistiocytosis (HLH) have been reported in patients treated with sulfamethoxazole-trimethoprim. HLH is a lifethreatening syndrome of pathologic immune activation characterized by clinical signs and symptoms of extreme systemic inflammation. Signs and symptoms of HLH may include fever, hepatosplenomegaly, rash, lymphadenopathy, neurologic symptoms, cytopenias, high serum ferritin, hypertriglyceridemia, and liver enzyme and coagulation abnormalities. If HLH is suspected, discontinue Sulfamethoxazole and trimethoprim oral suspension immediately and institute appropriate management.

Thrombocytopenia

Sulfamethoxazole and trimethoprim-induced thrombocytopenia may be an immune-mediated disorder. Severe cases of thrombocytopenia that are fatal or life threatening have been reported. Thrombocytopenia usually resolves within a week upon discontinuation of sulfamethoxazole and trimethoprim.

Streptococcal Infections and Rheumatic Fever

The sulfonamides should not be used for treatment of group A β-hemolytic streptococcal infections. In an established infection, they will not eradicate the streptococcus and, therefore, will not prevent sequelae such as rheumatic fever.

Clostridioides difficile Associated Diarrhea

Clostridioides difficile associated diarrhea (CDAD) has been reported with use of nearly all antibacterial agents, including sulfamethoxazole and trimethoprim, and may range in severity from mild diarrhea to fatal colitis. Treatment with antibacterial agents alters the normal flora of the colon leading to overgrowth of C. difficile.

C. difficile produces toxins A and B which contribute to the development of CDAD. Hypertoxin producing strains of C. difficile cause increased morbidity and mortality, as these infections can be refractory to antimicrobial therapy and may require colectomy. CDAD must be considered in all patients who present with diarrhea following antibiotic use. Careful medical history is necessary since CDAD has been reported to occur over two months after the administration of antibacterial agents.

If CDAD is suspected or confirmed, ongoing antibiotic use not directed against C. difficile may need to be discontinued. Appropriate fluid and electrolyte management, protein supplementation, antibiotic treatment of C. difficile, and surgical evaluation should be instituted as clinically indicated.

Risk Associated with Concurrent Use of Leucovorin for Pneumocystis jirovecii Pneumonia

Treatment failure and excess mortality were observed when sulfamethoxazole and trimethoprim was used concomitantly with leucovorin for the treatment of HIV positive patients with P. jirovecii pneumonia in a randomized placebo-controlled trial.^4 Avoid coadministration of sulfamethoxazole and trimethoprim and leucovorin during treatment of P. jirovecii pneumonia.

PRECAUTIONS

Development of Drug Resistant Bacteria

Prescribing sulfamethoxazole and trimethoprim oral suspension in the absence of a proven or strongly suspected bacterial infection or a prophylactic indication is unlikely to provide benefit to the patient and increases the risk of the development of drug-resistant bacteria.

Folate Deficiency

Avoid use of sulfamethoxazole and trimethoprim in patients with impaired renal or hepatic function, in those with possible folate deficiency (e.g., the elderly, chronic alcoholics, patients receiving anticonvulsant therapy, patients with malabsorption syndrome, and patients in malnutrition states) and in those with severe allergies or bronchial asthma.

Hematological changes indicative of folic acid deficiency may occur in elderly patients or in patients with preexisting folic acid deficiency or kidney failure. These effects are reversible by folinic acid therapy (see PRECAUTIONS, Geriatric Use).

Hemolysis

In glucose-6-phosphate dehydrogenase deficient individuals, hemolysis may occur. This reaction is frequently dose-related.

Hypoglycemia

Cases of hypoglycemia in non-diabetic patients treated with sulfamethoxazole and trimethoprim are seen rarely, usually occurring after a few days of therapy. Patients with renal dysfunction, liver disease, malnutrition or those receiving high doses of sulfamethoxazole and trimethoprim are particularly at risk.

Impaired Phenylalanine Metabolism

The trimethoprim component of sulfamethoxazole and trimethoprim has been noted to impair phenylalanine metabolism, but this is of no significance in phenylketonuric patients on appropriate dietary restriction.

Porphyria and Hypothyroidism

Like other drugs containing sulfonamides, sulfamethoxazole and trimethoprim can precipitate porphyria crisis and hypothyroidism. Avoid use of sulfamethoxazole and trimethoprim in patients with porphyria or thyroid dysfunction.

Potential Risk in the Treatment of Pneumocystis jirovecii Pneumonia in Patients with Acquired Immunodeficiency Syndrome (AIDS)

AIDS patients may not tolerate or respond to sulfamethoxazole and trimethoprim in the same manner as non-AIDS patients. The incidence of adverse reactions, particularly rash, fever, leukopenia and elevated aminotransferase (transaminase) values, with sulfamethoxazole and trimethoprim therapy in AIDS patients who are being treated for P. jiroveciipneumonia has been reported to be increased compared with the incidence normally associated with the use of sulfamethoxazole and trimethoprim in non-AIDS patients. If a patient develops skin rash, fever, leukopenia or any sign of adverse reaction, reevaluate benefit-risk of continuing therapy or re-challenge with sulfamethoxazole and trimethoprim (see WARNINGS).

Avoid coadministration of sulfamethoxazole and trimethoprim and leucovorin during treatment of P. jirovecii pneumonia (see WARNINGS).

Electrolyte Abnormalities

Hyperkalemia: High dosage of trimethoprim, as used in patients with P. jirovecii pneumonia, induces a progressive but reversible increase of serum potassium concentrations in a substantial number of patients. Even treatment with recommended doses may cause hyperkalemia when trimethoprim is administered to patients with underlying disorders of potassium metabolism, with renal insufficiency, or if drugs known to induce hyperkalemia are given concomitantly. Close monitoring of serum potassium is warranted in these patients.

Hyponatremia: Severe and symptomatic hyponatremia can occur in patients receiving sulfamethoxazole and trimethoprim, particularly for the treatment of P. jirovecii pneumonia. Evaluation for hyponatremia and appropriate correction is necessary in symptomatic patients to prevent life-threatening complications.

Crystalluria: During treatment, ensure adequate fluid intake and urinary output to prevent crystalluria. Patients who are “slow acetylators” may be more prone to idiosyncratic reactions to sulfonamides.

Information for Patients

Hypersensitivity and Other Serious Reactions: Advise patients to stop taking sulfamethoxazole and trimethoprim oral suspension immediately if they experience any clinical signs such as rash, pharyngitis, fever, arthralgia, cough, chest pain, dyspnea, pallor, purpura or jaundice and to contact their healthcare provider as soon as possible (see WARNINGSand ADVERSE REACTIONS).

Antibacterial Resistance: Patients should be counseled that antibacterial drugs including sulfamethoxazole and trimethoprim oral suspension should only be used to treat bacterial infections. They do not treat viral infections (e.g., the common cold). When sulfamethoxazole and trimethoprim oral suspension is prescribed to treat a bacterial infection, patients should be told that although it is common to feel better early in the course of therapy, the medication should be taken exactly as directed. Skipping doses or not completing the full course of therapy may (1) decrease the effectiveness of the immediate treatment and (2) increase the likelihood that bacteria will develop resistance and will not be treatable by sulfamethoxazole and trimethoprim oral suspension or other antibacterial drugs in the future.

Crystalluria and Stone Formation: Advise patients to maintain an adequate fluid intake in order to prevent crystalluria and stone formation.

Diarrhea: Advise patients that diarrhea is a common problem caused by antibiotics which usually ends when the antibiotic is discontinued. Sometimes after starting treatment with antibiotics, patients can develop watery and bloody stools (with or without stomach cramps and fever) even as late as two or more months after having taken the last dose of the antibiotic.If this occurs, patients should contact their physician as soon as possible.

Laboratory Tests

Complete blood counts and clinical chemistry testing should be done frequently in patients receiving sulfamethoxazole and trimethoprim. Perform urinalyses with careful microscopic examination and renal function tests during therapy, particularly for those patients with impaired renal function. Discontinue sulfamethoxazole and trimethoprim if a significant electrolyte abnormality, renal insufficiency or reduction in the count of any formed blood element is noted.

Drug Interactions

Potential for sulfamethoxazole and trimethoprim to Affect Other Drugs

Trimethoprim is an inhibitor of CYP2C8 as well as OCT2 transporter. Sulfamethoxazole is an inhibitor of CYP2C9. Avoid coadministration of sulfamethoxazole and trimethoprim with drugs that are substrates of CYP2C8 and 2C9 or OCT2.

Table 1: Drug Interactions with Sulfamethoxazole and Trimethoprim

Drug(s) | Recommendation | Comments
Diuretics | Avoid concurrent use | In elderly patients concurrently receiving certain diuretics, primarily thiazides, an increased incidence of thrombocytopenia with purpura has been reported.
Warfarin | Monitor prothrombin time and INR | It has been reported that sulfamethoxazole and trimethoprim may prolong the prothrombin time in patients who are receiving the anticoagulant warfarin (a CYP2C9 substrate). This interaction should be kept in mind when sulfamethoxazole and trimethoprim is given to patients already on anticoagulant therapy, and the coagulation time should be reassessed.
Phenytoin | Monitor serum phenytoin levels | Sulfamethoxazole and trimethoprim may inhibit the hepatic metabolism of phenytoin (a CYP2C9 substrate). Sulfamethoxazole and trimethoprim, given at a common clinical dosage, increased the phenytoin half-life by 39% and decreased the phenytoin metabolic clearance rate by 27%. When administering these drugs concurrently, one should be alert for possible excessive phenytoin effect.
Methotrexate | Avoid concurrent use | Sulfonamides can also displace methotrexate from plasma protein binding sites and can compete with the renal transport of methotrexate, thus increasing free methotrexate concentrations.
Cyclosporine | Avoid concurrent use | There have been reports of marked but reversible nephrotoxicity with coadministration of sulfamethoxazole and trimethoprim and cyclosporine in renal transplant recipients.
Digoxin | Monitor serum digoxin levels | Increased digoxin blood levels can occur with concomitant sulfamethoxazole and trimethoprim therapy, especially in elderly patients.
Indomethacin | Avoid concurrent use | Increased sulfamethoxazole blood levels may occur in patients who are also receiving indomethacin.
Pyrimethamine | Avoid concurrent use | Occasional reports suggest that patients receiving pyrimethamine as malaria prophylaxis in doses exceeding 25 mg weekly may develop megaloblastic anemia if sulfamethoxazole and trimethoprim is prescribed.
Tricyclic Antidepressants (TCAs) | Monitor therapeutic response and adjust dose of TCA accordingly | The efficacy of tricyclic antidepressants can decrease when coadministered with sulfamethoxazole and trimethoprim.
Oral Hypoglycemics | Monitor blood glucose more frequently | Like other sulfonamide-containing drugs, sulfamethoxazole and trimethoprim potentiates the effect of oral hypoglycemic that are metabolized by CYP2C8 (e.g., pioglitazone, repaglinide, and rosiglitazone) or CYP2C9 (e.g., glipizide and glyburide) or eliminated renally via OCT2 (e.g., metformin). Additional monitoring of blood glucose may be warranted.
Amantadine | Avoid concurrent use | In the literature, a single case of toxic delirium has been reported after concomitant intake of sulfamethoxazole and trimethoprim and amantadine (an OCT2 substrate). Cases of interactions with other OCT2 substrates, memantine and metformin, have also been reported.
Angiotensin Converting Enzyme Inhibitors | Avoid concurrent use | In the literature, three cases of hyperkalemia in elderly patients have been reported after concomitant intake of sulfamethoxazole and trimethoprim and an angiotensin converting enzyme inhibitor.^5,6
Zidovudine | Monitor for hematologic toxicity | Zidovudine and sulfamethoxazole and trimethoprim are known to induce hematological abnormalities. Hence, there is potential for an additive myelotoxicity when coadministered.^7
Dofetilide | Concurrent administration is contraindicated | Elevated plasma concentrations of dofetilide have been reported following concurrent administration of trimethoprim and dofetilide. Increased plasma concentrations of dofetilide may cause serious ventricular arrhythmias associated with QT interval prolongation, including torsade de pointes.^8,9
Procainamide | Closely monitor for clinical and ECG signs of procainamide toxicity and/or procainamide plasma concentration if available | Trimethoprim increases the plasma concentrations of procainamide and its active N-acetyl metabolite (NAPA) when trimethoprim and procainamide are coadministered. The increased procainamide and NAPA plasma concentrations that resulted from the pharmacokinetic interaction with trimethoprim are associated with further prolongation of the QTc interval.^10

Drug/Laboratory Test Interactions

Sulfamethoxazole and trimethoprim, specifically the trimethoprim component, can interfere with a serum methotrexate assay as determined by the competitive binding protein technique (CBPA) when a bacterial dihydrofolate reductase is used as the binding protein. No interference occurs, however, if methotrexate is measured by a radioimmunoassay (RIA).

The presence of sulfamethoxazole and trimethoprim may also interfere with the Jaffé alkaline picrate reaction assay for creatinine, resulting in overestimations of about 10% in the range of normal values.

Carcinogenesis, Mutagenesis, Impairment of Fertility

Carcinogenesis

Sulfamethoxazole was not carcinogenic when assessed in a 26-week tumorigenic mouse (Tg-rasH2) study at doses up to 400 mg/kg/day sulfamethoxazole; equivalent to 2.4-fold the human systemic exposure (at a daily dose of 800 mg sulfamethoxazole twice a day).

Mutagenesis

In vitro reverse mutation bacterial tests according to the standard protocol have not been performed with sulfamethoxazole and trimethoprim in combination. An in vitro chromosomal aberration test in human lymphocytes with sulfamethoxazole and trimethoprim was negative. In in vitro and in vivo tests in animal species, sulfamethoxazole and trimethoprim did not damage chromosomes. In vivo micronucleus assays were positive following oral administration of sulfamethoxazole and trimethoprim. Observations of leukocytes obtained from patients treated with sulfamethoxazole and trimethoprim revealed no chromosomal abnormalities.

Sulfamethoxazole alone was positive in an in vitro reverse mutation bacterial assay and in in vitro micronucleus assays using cultured human lymphocytes.

Trimethoprim alone was negative in in vitro reverse mutation bacterial assays and in in vitro chromosomal aberration assays with Chinese Hamster ovary or lung cells with or without S9 activation. In in vitro Comet, micronucleus and chromosomal damage assays using cultured human lymphocytes, trimethoprim was positive. In mice following oral administration of trimethoprim, no DNA damage in Comet assays of liver, kidney, lung, spleen, or bone marrow was recorded.

Impairment of Fertility

No adverse effects on fertility or general reproductive performance were observed in rats given oral dosages as high as 350 mg/kg/day sulfamethoxazole plus 70 mg/kg/day trimethoprim, doses roughly two times the recommended human daily dose on a body surface area basis.

Pregnancy

While there are no large, well-controlled studies on the use of sulfamethoxazole and trimethoprim in pregnant women, Brumfitt and Pursell,^11 in a retrospective study, reported the outcome of 186 pregnancies during which the mother received either placebo or sulfamethoxazole and trimethoprim. The incidence of congenital abnormalities was 4.5% (3 of 66) in those who received placebo and 3.3% (4 of 120) in those receiving sulfamethoxazole and trimethoprim. There were no abnormalities in the 10 children whose mothers received the drug during the first trimester. In a separate survey, Brumfitt and Pursell also found no congenital abnormalities in 35 children whose mothers had received oral sulfamethoxazole and trimethoprim at the time of conception or shortly thereafter.

Because sulfamethoxazole and trimethoprim may interfere with folic acid metabolism, sulfamethoxazole and trimethoprim should be used during pregnancy only if the potential benefit justifies the potential risk to the fetus.

Teratogenic Effects

Human Data

While there are no large prospective, well controlled studies in pregnant women and their babies, some retrospective epidemiologic studies suggest an association between first trimester exposure to sulfamethoxazole and trimethoprim with an increased risk of congenital malformations, particularly neural tube defects, cardiovascular abnormalities, urinary tract defects, oral clefts, and club foot. These studies, however, were limited by the small number of exposed cases and the lack of adjustment for multiple statistical comparisons and confounders. These studies are further limited by recall, selection, and information biases, and by limited generalizability of their findings. Lastly, outcome measures varied between studies, limiting cross-study comparisons. Alternatively, other epidemiologic studies did not detect statistically significant associations between sulfamethoxazole and trimethoprim exposure and specific malformations.

Animal Data

In rats, oral doses of either 533 mg/kg sulfamethoxazole or 200 mg/kg trimethoprim produced teratologic effects manifested mainly as cleft palates. These doses are approximately 5 and 6 times the recommended human total daily dose on a body surface area basis. In two studies in rats, no teratology was observed when 512 mg/kg of sulfamethoxazole was used in combination with 128 mg/kg of trimethoprim. In some rabbit studies, an overall increase in fetal loss (dead and resorbed conceptuses) was associated with doses of trimethoprim 6 times the human therapeutic dose based on body surface area.

Nonteratogenic Effects

See CONTRAINDICATIONSsection.

Nursing Mothers

Levels of sulfamethoxazole and trimethoprim in breast milk are approximately 2–5% of the recommended daily dose for infants over 2 months of age. Caution should be exercised when sulfamethoxazole and trimethoprim is administered to a nursing woman, especially when breastfeeding jaundiced, ill, stressed, or premature infants because of the potential risk of bilirubin displacement and kernicterus.

Pediatric Use

Sulfamethoxazole and trimethoprim is contraindicated for infants younger than 2 months of age (see INDICATIONS AND USAGEand CONTRAINDICATIONS).

Geriatric Use

Clinical studies of sulfamethoxazole and trimethoprim did not include sufficient numbers of subjects aged 65 and over to determine whether they respond differently from younger subjects.

There may be an increased risk of severe adverse reactions in elderly patients, particularly when complicating conditions exist, e.g., impaired kidney and/or liver function, possible folate deficiency, or concomitant use of other drugs. Severe skin reactions, generalized bone marrow suppression (see WARNINGSand ADVERSE REACTIONS), a specific decrease in platelets (with or without purpura), and hyperkalemia are the most frequently reported severe adverse reactions in elderly patients. In those concurrently receiving certain diuretics, primarily thiazides, an increased incidence of thrombocytopenia with purpura has been reported. Increased digoxin blood levels can occur with concomitant sulfamethoxazole and trimethoprim therapy, especially in elderly patients. Serum digoxin levels should be monitored. Hematological changes indicative of folic acid deficiency may occur in elderly patients. These effects are reversible by folinic acid therapy. Appropriate dosage adjustments should be made for patients with impaired kidney function and duration of use should be as short as possible to minimize risks of undesired reactions (see DOSAGE AND ADMINISTRATION). The trimethoprim component of sulfamethoxazole and trimethoprim may cause hyperkalemia when administered to patients with underlying disorders of potassium metabolism, with renal insufficiency or when given concomitantly with drugs known to induce hyperkalemia, such as angiotensin converting enzyme inhibitors. Close monitoring of serum potassium is warranted in these patients. Discontinuation of sulfamethoxazole and trimethoprim treatment is recommended to help lower potassium serum levels.

Pharmacokinetics parameters for sulfamethoxazole were similar for geriatric subjects and younger adult subjects. The mean maximum serum trimethoprim concentration was higher and mean renal clearance of trimethoprim was lower in geriatric subjects compared with younger subjects (see CLINICAL PHARMACOLOGY: Geriatric Pharmacokinetics).

ADVERSE REACTIONS

The following adverse reactions associated with the use of sulfamethoxazole and trimethoprim were identified in clinical trials, postmarketing or published reports. Because some of these reactions were reported voluntarily from a population of uncertain size, it is not always possible to reliably estimate their frequency or establish a causal relationship to drug exposure.

The most common adverse reactions are gastrointestinal disturbances (nausea, vomiting, anorexia) and allergic skin reactions (such as rash and urticaria). Fatalities and serious adverse reactions, including severe cutaneous adverse reactions (SCARs), including Stevens-Johnson syndrome, toxic epidermal necrolysis, drug reaction with eosinophilia and systemic symptoms (DRESS), acute febrile neutrophilic dermatosis (AFND), acute generalized erythematous pustulosis (AGEP); fulminant hepatic necrosis; agranulocytosis, aplastic anemia and other blood dyscrasias; acute and delayed lung injury; anaphylaxis and circulatory shock have occurred with the administration of sulfamethoxazole and trimethoprim products, including sulfamethoxazole and trimethoprim (see WARNINGS).

Hematologic: Agranulocytosis, aplastic anemia, thrombocytopenia, leukopenia, neutropenia, hemolytic anemia, megaloblastic anemia, hypoprothrombinemia, methemoglobinemia, eosinophilia, thrombotic thrombocytopenic purpura, idiopathic thrombocytopenic purpura.

Allergic/ Immune Reactions: Stevens-Johnson syndrome, toxic epidermal necrolysis, anaphylaxis, allergic myocarditis, erythema multiforme, exfoliative dermatitis, angioedema, drug fever, chills, Henoch-Schöenlein purpura, serum sickness-like syndrome, generalized allergic reactions, generalized skin eruptions, photosensitivity, conjunctival and scleral injection, pruritus, urticaria, rash, periarteritis nodosa, hemophagocytic lymphohistiocytosis (HLH), systemic lupus erythematosus, drug reaction with eosinophilia and systemic symptoms (DRESS), acute generalized erythematous pustulosis (AGEP), and acute febrile neutrophilic dermatosis (AFND) (see WARNINGS).

Gastrointestinal: Hepatitis (including cholestatic jaundice and hepatic necrosis), elevation of serum transaminase and bilirubin, pseudomembranous enterocolitis, pancreatitis, stomatitis, glossitis, nausea, emesis, abdominal pain, diarrhea, anorexia.

Genitourinary: Renal failure, interstitial nephritis, BUN and serum creatinine elevation, renal insufficiency, oliguria and anuria, crystalluria and nephrotoxicity in association with cyclosporine.

Metabolic and Nutritional: Hyperkalemia, hyponatremia (see PRECAUTIONS: Electrolyte Abnormalities), metabolic acidosis.

Neurologic: Aseptic meningitis, convulsions, peripheral neuritis, ataxia, vertigo, tinnitus, headache.

Psychiatric: Hallucinations, depression, apathy, nervousness.

Endocrine: The sulfonamides bear certain chemical similarities to some goitrogens, diuretics (acetazolamide and the thiazides) and oral hypoglycemic agents. Cross-sensitivity may exist with these agents. Diuresis and hypoglycemia have occurred.

Musculoskeletal: Arthralgia, myalgia, rhabdomyolysis.

Respiratory: Cough, shortness of breath and pulmonary infiltrates, acute eosinophilic pneumonia, acute and delayed lung injury, interstitial lung disease, acute respiratory failure (see WARNINGS).

Cardiovascular System: QT prolongation resulting in ventricular tachycardia and torsades de pointes, circulatory shock (see WARNINGS).

Miscellaneous: Weakness, fatigue, insomnia.

OVERDOSAGE

Acute

The amount of a single dose of sulfamethoxazole and trimethoprim that is either associated with symptoms of overdosage or is likely to be life-threatening has not been reported. Signs and symptoms of overdosage reported with sulfonamides include anorexia, colic, nausea, vomiting, dizziness, headache, drowsiness and unconsciousness. Pyrexia, hematuria and crystalluria may be noted. Blood dyscrasias and jaundice are potential late manifestations of overdosage.

Signs of acute overdosage with trimethoprim include nausea, vomiting, dizziness, headache, mental depression, confusion and bone marrow depression.

General principles of treatment include the institution of gastric lavage or emesis, forcing oral fluids, and the administration of intravenous fluids if urine output is low and renal function is normal. Acidification of the urine will increase renal elimination of trimethoprim. The patient should be monitored with blood counts and appropriate blood chemistries, including electrolytes. If a significant blood dyscrasia or jaundice occurs, specific therapy should be instituted for these complications. Peritoneal dialysis is not effective and hemodialysis is only moderately effective in eliminating sulfamethoxazole and trimethoprim.

Chronic

Use of sulfamethoxazole and trimethoprim at high doses and/or for extended periods of time may cause bone marrow depression manifested as thrombocytopenia, leukopenia and/or megaloblastic anemia. If signs of bone marrow depression occur, the patient should be given leucovorin 5 to 15 mg daily until normal hematopoiesis is restored.

DOSAGE AND ADMINISTRATION

Sulfamethoxazole and trimethoprim oral suspension is contraindicated in pediatric patients less than 2 months of age.

Urinary Tract Infections and Shigellosis in Adults and Pediatric Patients, and Acute Otitis Media in Children

Adults: The usual adult dosage in the treatment of urinary tract infections is 4 teaspoonfuls (20 mL) of sulfamethoxazole and trimethoprim oral suspension every 12 hours for 10 to 14 days. An identical daily dosage is used for 5 days in the treatment of shigellosis.

Children: The recommended dose for children with urinary tract infections or acute otitis media is 40 mg/kg sulfamethoxazole and 8 mg/kg trimethoprim per 24 hours, given in two divided doses every 12 hours for 10 days. An identical daily dosage is used for 5 days in the treatment of shigellosis. The following table is a guideline for the attainment of this dosage:

Children 2 months of age or older:

Weight |  | Dose - every 12 hours
lb | kg | Teaspoonfuls
22 | 10 | 1 (5 mL)
44 | 20 | 2 (10 mL)
66 | 30 | 3 (15 mL)
88 | 40 | 4 (20 mL)

For Patients with Impaired Renal Function

When renal function is impaired, a reduced dosage should be employed using the following table:

Creatinine Clearance (mL/min) | Recommended Dosage Regimen
Above 30 | Usual standard regimen
15-30 | ½ the usual regimen
Below 15 | Use not recommended

Acute Exacerbations of Chronic Bronchitis in Adults

The usual adult dosage in the treatment of acute exacerbations of chronic bronchitis is 4 teaspoonfuls (20 mL) sulfamethoxazole and trimethoprim oral suspension every 12 hours for 14 days.

Pneumocystis jirovecii Pneumonia

Treatment

Adults and Children:

The recommended dosage for treatment of patients with documented Pneumocystis jiroveciipneumonia is 75 to 100 mg/kg sulfamethoxazole and 15 to 20 mg/kg trimethoprim per 24 hours given in equally divided doses every 6 hours for 14 to 21 days.^12 The following table is a guideline for the upper limit of this dosage:

Weight |  | Dose - every 6 hours
lb | kg | Teaspoonfuls
18 | 8 | 1 (5 mL)
35 | 16 | 2 (10 mL)
53 | 24 | 3 (15 mL)
70 | 32 | 4 (20 mL)
88 | 40 | 5 (25 mL)
108 | 48 | 6 (30 mL)
141 | 64 | 8 (40 mL)
176 | 80 | 10 (50 mL)

For the lower limit dose (75 mg/kg sulfamethoxazole and 15 mg/kg trimethoprim per 24 hours) administer 75% of the dose in the above table.

Prophylaxis

Adults:

The recommended dosage for prophylaxis in adults is 4 teaspoonfuls (20 mL) of sulfamethoxazole and trimethoprim oral suspension daily.^13

Children:

For children, the recommended dose is 750 mg/m^2/day sulfamethoxazole with 150 mg/m^2/day trimethoprim given orally in equally divided doses twice a day, on 3 consecutive days per week. The total daily dose should not exceed 1,600 mg sulfamethoxazole and 320 mg trimethoprim.^14 The following table is a guideline for the attainment of this dosage in children:

Body Surface Area | Dose - every 12 hours
(m^2) | Teaspoonfuls
0.26 | ½ (2.5 mL)
0.53 | 1 (5 mL)
1.06 | 2 (10 mL)

Traveler’s Diarrhea in Adults

For the treatment of traveler’s diarrhea, the usual adult dosage is 4 teaspoonfuls (20 mL) of sulfamethoxazole and trimethoprim oral suspension every 12 hours for 5 days.

HOW SUPPLIED

Sulfamethoxazole and Trimethoprim Oral Suspension, USP (Cherry Flavor), opaque, pinkish orange suspension with a cherry aroma, containing 40 mg trimethoprim and 200 mg sulfamethoxazole in each teaspoonful (5 mL), and is available in a 20 mL Unit-Dose cup NDC 68999-873-52 and 20 Unit-Dose Cups of 20 mL each NDC 68999-873-24.

Store at 20° to 25°C (68° to 77°F) [see USP Controlled Room Temperature] and protect from light.

To report SUSPECTED ADVERSE REACTIONS, contact Chartwell Governmental & Specialty RX, LLC. at 1-845-232-1683 or FDA at 1-800-FDA-1088 or www.fda.gov/medwatch.

REFERENCES

1. Kremers P, Duvivier J, Heusghem C. Pharmacokinetic Studies of Co-Trimoxazole in Man after Single and Repeated Doses. J Clin Pharmacol. Feb-Mar 1974;14:112–117.

2. Kaplan SA, et al. Pharmacokinetic Profile of Trimethoprim-Sulfamethoxazole in Man. J Infect Dis. Nov 1973; 128 (Suppl): S547–S555.

3. Varoquaux O, et al. Pharmacokinetics of the trimethoprim-sulfamethoxazole combination in the elderly. Br J Clin Pharmacol. 1985;20:575–581.

4. Safrin S, Lee BL, Sande MA. Adjunctive folinic acid with trimethoprim-sulfamethoxazole for Pneumocystis cariniipneumonia in AIDS patients is associated with an increased risk of therapeutic failure and death. J Infect Dis. 1994 Oct;170(4):912–7.

5. Marinella Mark A. 1999. Trimethoprim-induced hyperkalemia: An analysis of reported cases. Gerontol. 45:209–212.

6. Margassery, S. and B. Bastani. 2002. Life threatening hyperkalemia and acidosis secondary to trimethoprim-sulfamethoxazole treatment. J. Nephrol.14:410–414.

7. Moh R, et al. Haematological changes in adults receiving a zidovudine-containing HAART regimen in combination with cotrimoxazole in Côte d'Ivoire. Antivir Ther. 2005;10(5):615-24.

8. Al-Khatib SM, LaPointe N, Kramer JM, Califf RM. What Clinicians Should Know About the QT Interval. JAMA. 2003;289(16):2120-2127.

9. Boyer EW, Stork C, Wang RY. Review: The Pharmacology and Toxicology of Dofetilide. Int J Med Toxicol. 2001;4(2):16.

10. Kosoglou T, Rocci ML Jr, Vlasses PH. Trimethoprim alters the disposition of procainamide and N-acetylprocainamide. Clin Pharmacol Ther. Oct 1988;44(4):467-77.

11. Brumfitt W, Pursell R. Trimethoprim/Sulfamethoxazole in the Treatment of Bacteriuria in Women. J Infect Dis. Nov 1973; 128 (Suppl): S657–S663.

12. Masur H. Prevention and treatment of Pneumocystispneumonia. N Engl J Med.1992; 327: 1853–1880.

13. Recommendations for prophylaxis against Pneumocystis cariniipneumonia for adults and adolescents infected with human immunodeficiency virus. MMWR. 1992; 41(RR-4):1–11.

14. CDC Guidelines for prophylaxis against Pneumocystis cariniipneumonia for children infected with human immunodeficiency virus. MMWR. 1991; 40(RR-2):1–13.

All trademarks are the property of their respective owners.

Manufactured for:
Chartwell Governmental & Specialty RX, LLC.
Congers, NY 10920

L72919

Rev. 02/2026

PACKAGE LABEL.PRINCIPAL DISPLAY PANEL

Sulfamethoxazole and Trimethoprim Oral Suspension, USP 800 mg/160 mg per 20 mL - NDC 68999-873-52 - 20 mL Unit Dose Cup Label